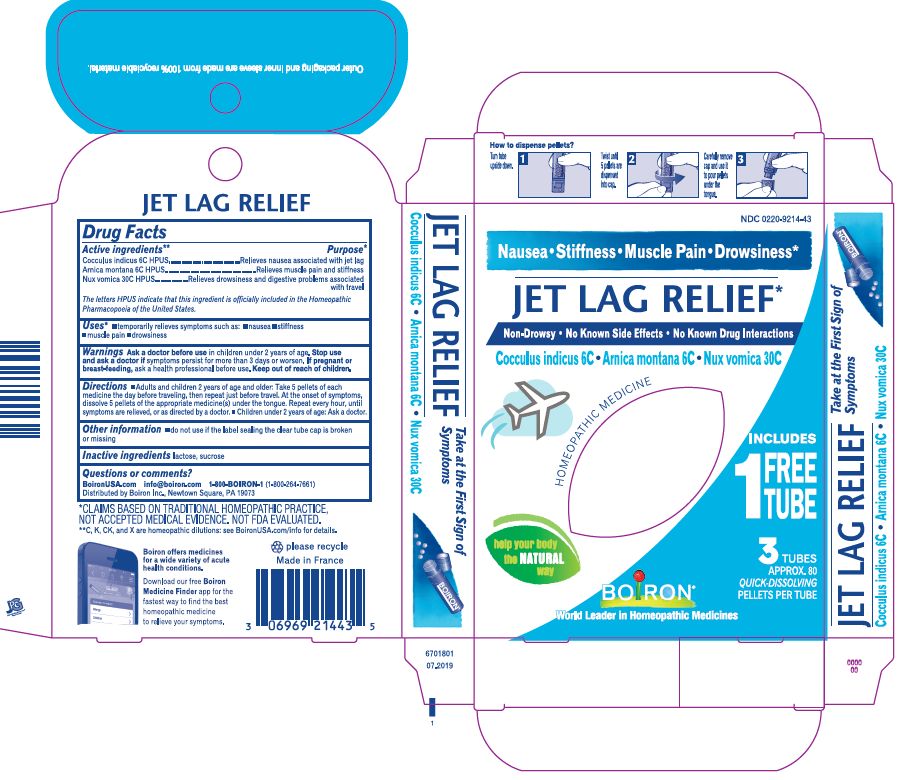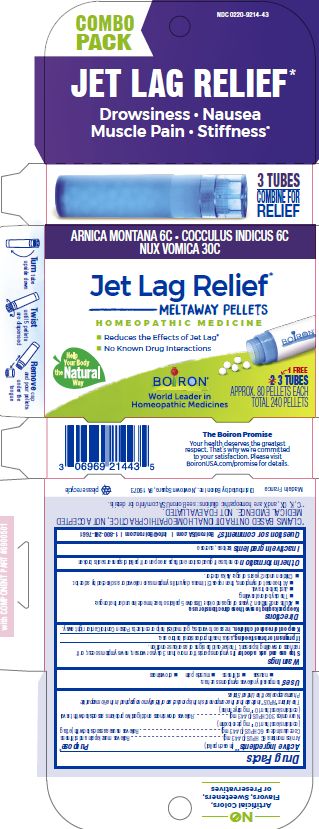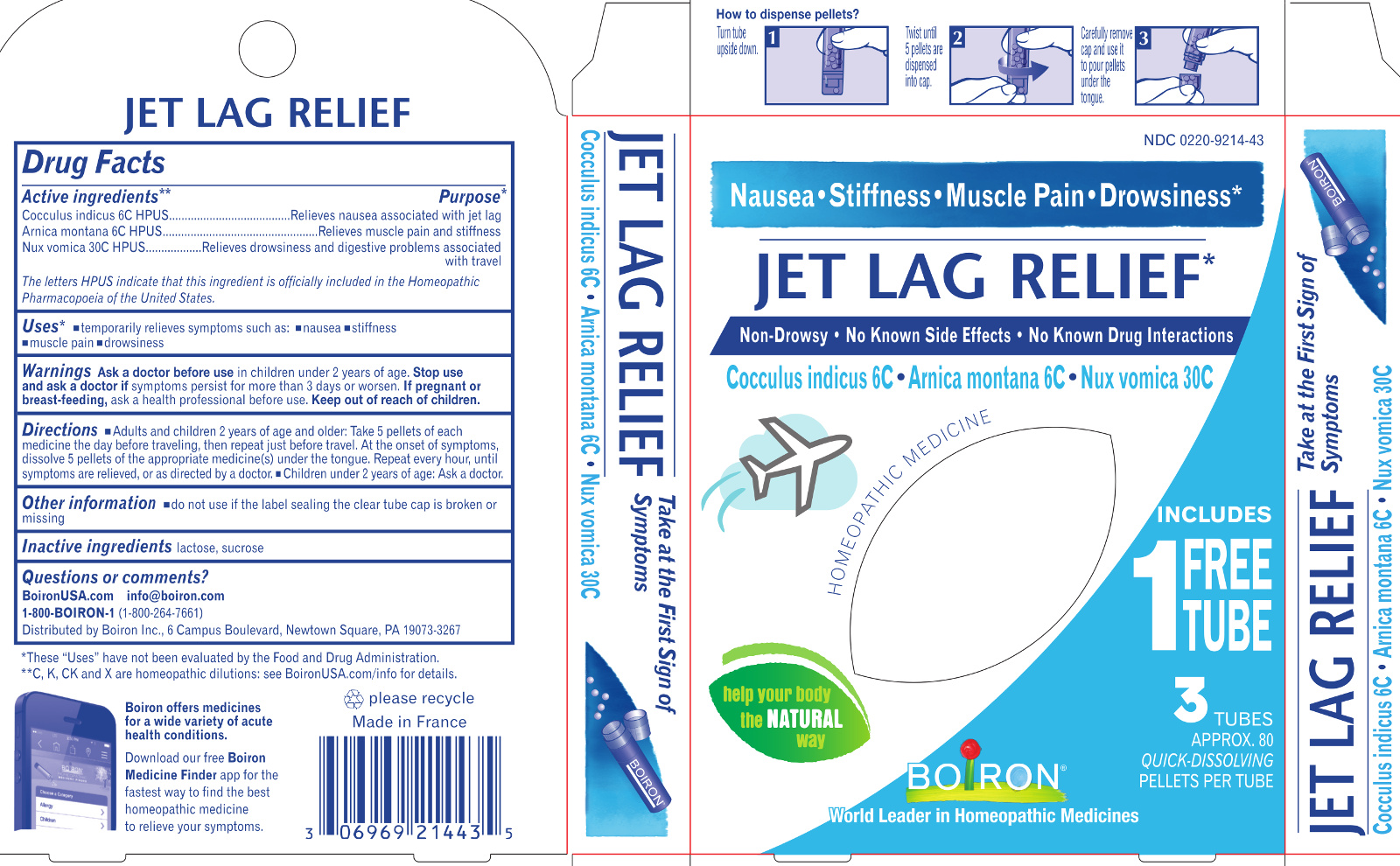 DRUG LABEL: Jet Lag Relief
NDC: 0220-9214 | Form: PELLET
Manufacturer: Laboratoires Boiron
Category: homeopathic | Type: HUMAN OTC DRUG LABEL
Date: 20231004

ACTIVE INGREDIENTS: ANAMIRTA COCCULUS SEED 6 [hp_C]/1 1; ARNICA MONTANA 6 [hp_C]/1 1; STRYCHNOS NUX-VOMICA WHOLE 30 [hp_C]/1 1
INACTIVE INGREDIENTS: SUCROSE; LACTOSE

Jet Lag Relief

Active Ingredients** (in each pellet)

Cocculus indicus 6C HPUS (0.443 mg)
Arnica montana 6C HPUS (0.443 mg) (contains less than 10^-12 mg picrotoxinin)
Nux Vomica 30C HPUS (0.443 mg) (contains less than 10^-12 mg strychnine)
The letters "HPUS" indicate that this ingredient is officially included in the Homeopathic Pharmacopoeia of the United States.

Purpose*

Cocculus indicus 6C HPUS (0.443 mg) ..... Relieves nausea associated with jet lag
Arnica montana 6C HPUS (0.443 mg) ..... Relieves muscle pain and stiffness
Nux Vomica 30C HPUS (0.443 mg) ..... Relieves drowsiness and digestive problems associated with travel

Uses*

temporarily relieves symptoms such as:

- nausea
- stiffness
- muscle pain
- drowsiness

WARNINGS

Stop use and ask a doctor if symptoms persist for more than 3 days or worsen, new symptoms occur, or if redness or swelling if present. These could be signs of a serious condition.

PREGNANCY OR BREAST FEEDING

If pregnant or breast-feeding, ask a health professional before use.

Keep out of reach of children. In case of overdose, get medical help or contact a Poison Control Center right away.

Directions

Keep packaging to save these directions for use.

Adults and children 2 years of age and older: Dissolve 5 pellets of each medicine under the tongue:

- The day before traveling.
- Just before travel.
- At the onset of symptoms, then repeat 3 times a day until symptoms are relieved or as directed by a doctor.

Children under 2 years of age: Ask a doctor.

Inactive ingredients

lactose, sucrose

do not use if glued carton and flaps are open or if pellet dispenser seal is broken

Jet Lag Relief*

Drowsiness Nausea Muscle Pain Stiffness*

Reduces the effects of Jet Lag*

No Know Drug Interactions

3 Tubes combine for relief

3 Tubes

Approx. 80 Pellets Each

Total 240 Pellets

Turn tube upside down Twist until 5 pellets are dispensed Remove cap and pour pellets under the tongue

*CLAIMS BASED ON TRADITIONAL HOMEOPATHIC PRACTICE, NOT ACCEPTED MEDICAL EVIDENCE. NOT FDA EVALUATED.
**C,K,CK, and X are homeopathic dilutions: see BoironUSA.com/info for details.

Questions, Comments?

Questions or comments?

BoironUSA.com
info@boiron.com
1-800-BOIRON-1 (1-800-264-7661)
Distributed by Boiron Inc.

Newtown Square, PA 19073-3267